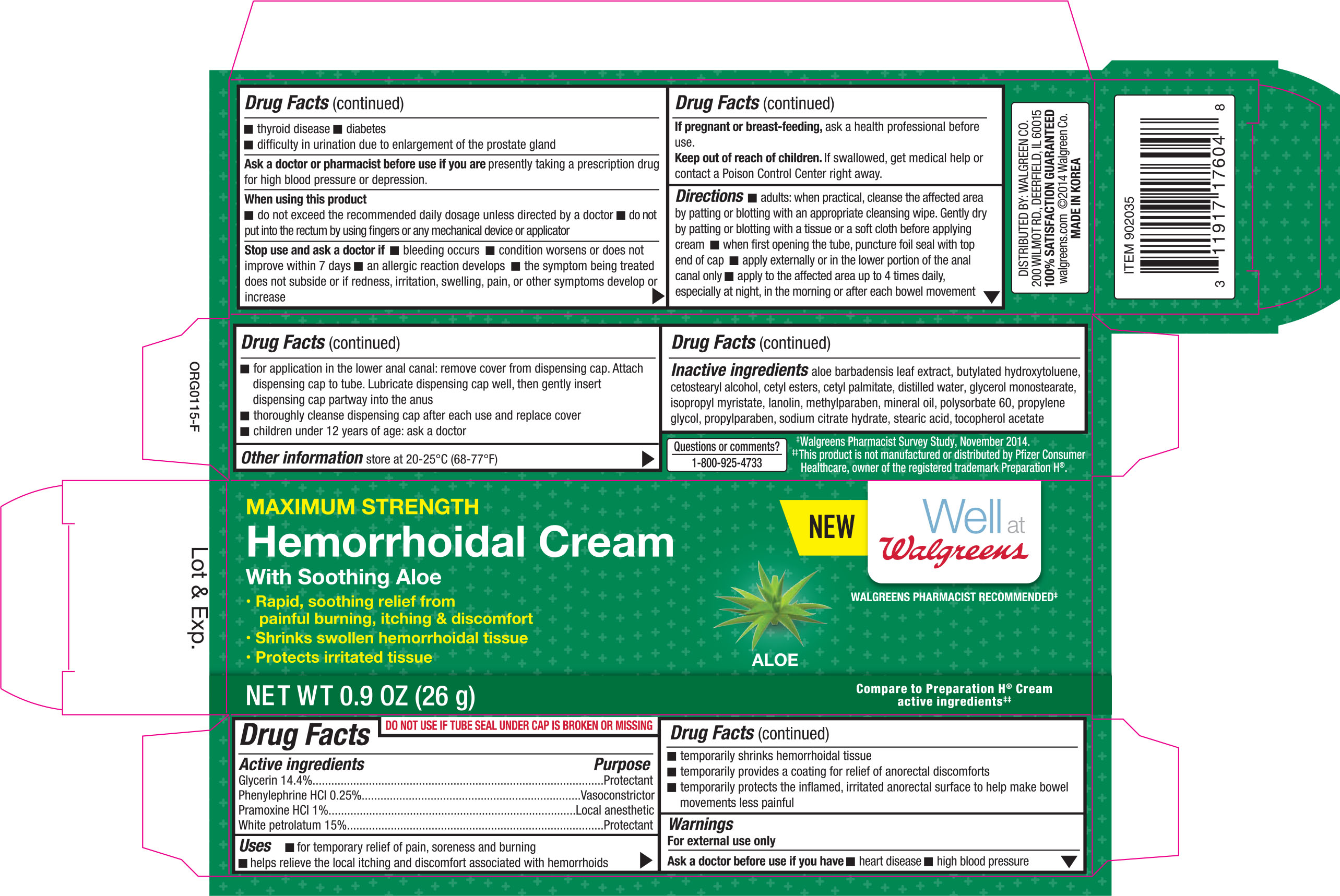 DRUG LABEL: Walgreens Maximum Strength Hemorrhoidal
NDC: 0363-1760 | Form: CREAM
Manufacturer: Walgreen Company
Category: otc | Type: HUMAN OTC DRUG LABEL
Date: 20181207

ACTIVE INGREDIENTS: GLYCERIN 0.144 mg/1 g; PHENYLEPHRINE HYDROCHLORIDE 0.0025 mg/1 g; PRAMOXINE HYDROCHLORIDE 0.01 mg/1 g; PETROLATUM 0.15 mg/1 g
INACTIVE INGREDIENTS: ALOE VERA LEAF; BUTYLATED HYDROXYTOLUENE; CETOSTEARYL ALCOHOL; CETYL ESTERS WAX; CETYL PALMITATE; WATER; GLYCERYL MONOSTEARATE; ISOPROPYL MYRISTATE; LANOLIN; METHYLPARABEN; MINERAL OIL; POLYSORBATE 60; PROPYLENE GLYCOL; PROPYLPARABEN; TRISODIUM CITRATE DIHYDRATE; STEARIC ACID; .ALPHA.-TOCOPHEROL ACETATE

Walgreens Hemorrhoidal Cream 0.9OZ (with applicator) 902035 (2018)

Active ingredients Purpose

Glycerin 14.4%.................................................................................. Protectant

Phenylephrine HCL 0.25%................................................................... Vasoconstrictor

Pramoxine HCL 1%............................................................................. Local anaesthetic

White petrolatum 15%......................................................................... Protectant

Uses

- for temporary relief of pain, soreness and burning
- helps relieve the local itching and discomfort associated with hemorrhoids
- temporarily shrinks hemorrhoidal tissue
- temporarily provides a coating for relief of anorectal discomforts
- temporarily protects the inflamed, irritated anorectal surface to help make bowel movements less painful

Warnings

For external use only

Ask a doctor before use if you have

- heart disease
- high blood pressure
- thyroid disease
- diabetes
- difficult in urination due to enlargement of the prostate gland

Ask a doctor or pharmacist before use if you are presently taking a prescription drug for high blood pressure or depression

When using this product

- do not exceed the recommended daily dosage unless directed by a doctor
- do not put into the rectum by using fingers or any mechanical device or applicator

Stop use and ask a doctor if

- bleeding occurs
- condition worsens or does not improve within 7 days
- an allergic reaction develops
- the symptoms being treated does not subside or if redness, irritation, swelling, pain, or other symptoms develop or increase

PREGNANCY OR BREAST FEEDING

If pregnant or breask-feeding, ask a health professional before use

Keep out of reach of children. If swallowed, get medical help or contact a Poison Control Center right away

Directions

- adults: when practical, cleanse the affected area by patting or blotting with an appropriate cleansing wipe. Gently dry by patting or blotting with a tissue or a soft cloth before applying cream
- when first opening the tube, puncture foil seal with top end of cap
- apply externally or in the lower portion of the anal canal only
- apply to the affected area up to 4 times daily, especially at night, in the morning or after each bowel movement
- for application in the lower anal canal: remove cover from dispensing cap. Attach dispensing cap to tube. Lubricate dispensing cap well, then gently insert dispensing cap partway into the anus
- thoroughly cleanse dispensing cap after each use and replace cover
- children under 12 years of age: ask a doctor

Other information

store at 20-25°C (68-77°F)

Inactive ingredients

aloe barbadensis leaf extract, butylated hydroxytoluene, cetostearyl alcohol, cetyl esters, cetyl palmitate, distilled water, glycerol monostearate, isopropyl myristate, lanolin, methylparaben, mineral oil, polysorbate 60, propylene glycol, propylparaben, sodium citrate hydrate, stearic acid, tocopherol acetate

DOSAGE AND ADMINISTRATION

DISTRIBUTED BY:

WALLGREEN CO.

200 WILMOT RD.

DEERFIELD, IL 60015

MADE IN KOREA